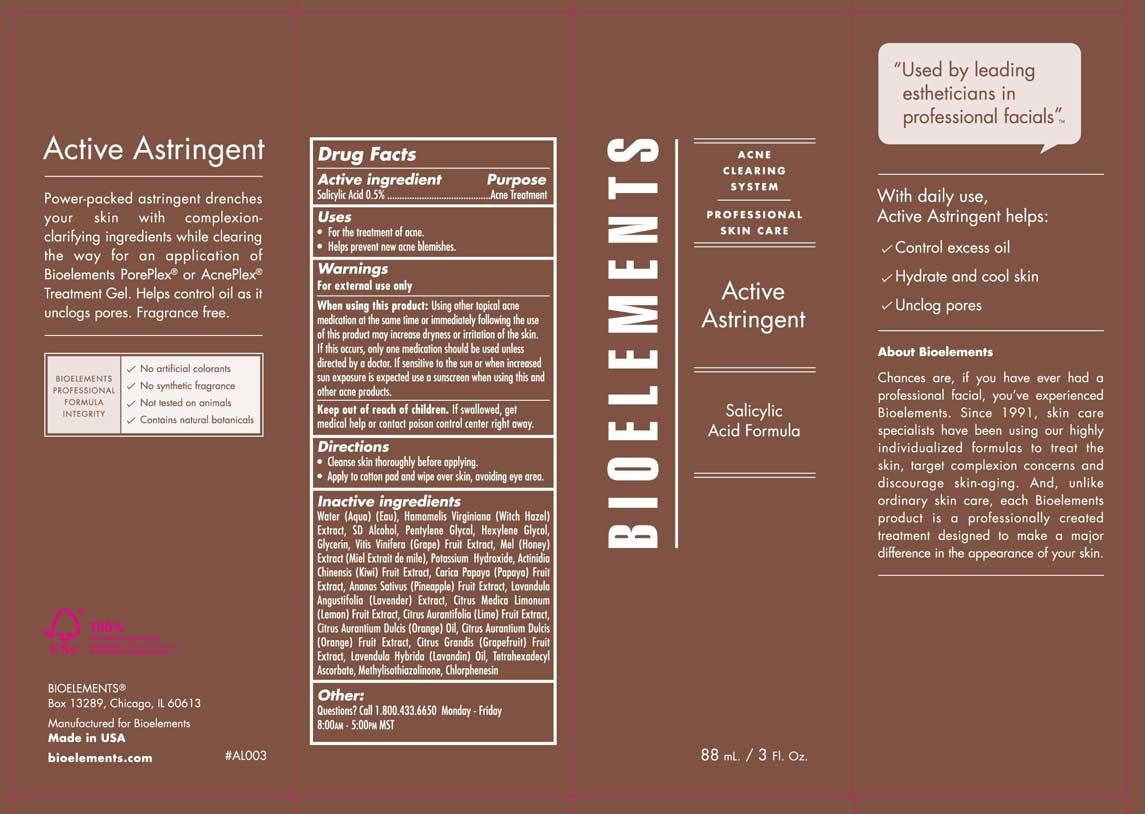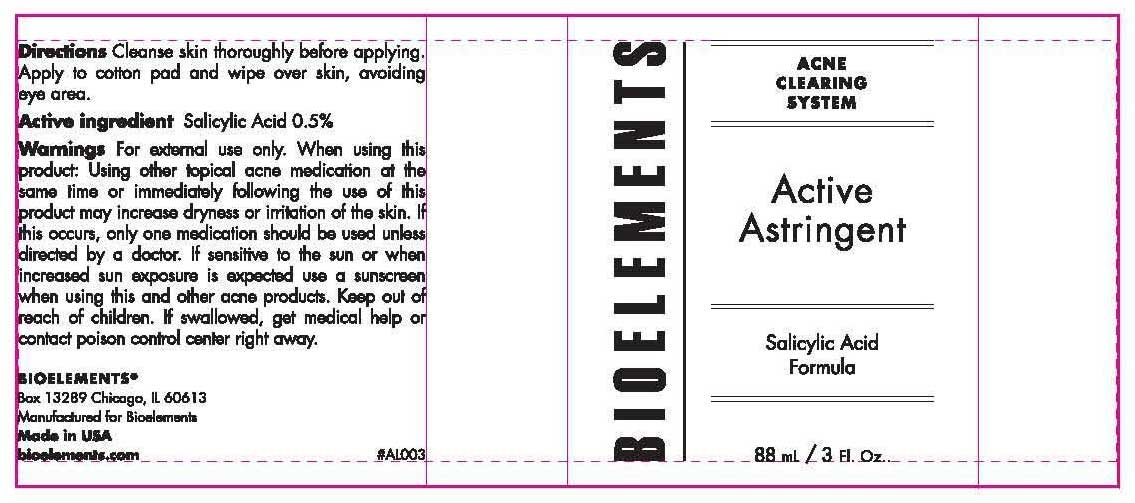 DRUG LABEL: Bioelements
NDC: 49825-111 | Form: LIQUID
Manufacturer: Bioelements
Category: prescription | Type: HUMAN PRESCRIPTION DRUG LABEL
Date: 20100611

ACTIVE INGREDIENTS: SALICYLIC ACID 0.5 mL/100 mL

Active Astringent

Active Ingredients Purpose

Salicylic Acid 0.5% Acne Treatment

Uses:

-For the treatment of acne

-Helps prevent new acne blemishes

Directions

-Cleanse skin thoroughly before applying

-Apply to cotton pad and wipe over skin, avoiding eye area.

Warnings

-For external use only

-When using this product: Using other topical acne medication at the same time or immediately following the use of this product may increase dryness or irritation of the skin. If this occurs, only one medication should be used unless directed by a doctor. If sensitive to the sun or when increased sun exposure is expected use a sunscreen when using this and other acne products.

-Keep out of reach of children. If swallowed, get medical help or contact poison center right away.

INACTIVE INGREDIENT

Inactive Ingredients: Water (Aqua) (Eau), Hamamelis Virginiana (Witch Hazel) Extract, SD Alcohol, Pentylene Glycol, Hexylene Glycol, Glycerin, Vitis Vinifera (Grape) Fruit Extract, Mel (Honey) Extract (Miel Extrait de mile), Potassium Hydroxide, Actinidia Chinensis (Kiwi) Fruit Extract, Carica Papaya (Papaya) Fruit Extract, Anenas Sativus (Pineapple) Fruit Extract, Lavandula Angustifolia (Lavender) Extract, Citrus Medica Limonum (Lemon) Fruit Extract, Citrus Aurantifolia (Lime) Fruit Extract, Citrus Aurantium Dulcis (Orange) Oil, Citrus Aurantium Dulcis (Orange) Fruit Extract, Citrus Grandis (Grapefruit) Fruit Extract, Lavendula Hybrida (Lavandin) Oil, Tetrahexadecyl Ascorbate, Methylisothiazolinone, Chlorphenesin

PACKAGE LABEL

Bioelements

Acne Clearing System

Active Astringent

88 mL. / 3 Fl. Oz.